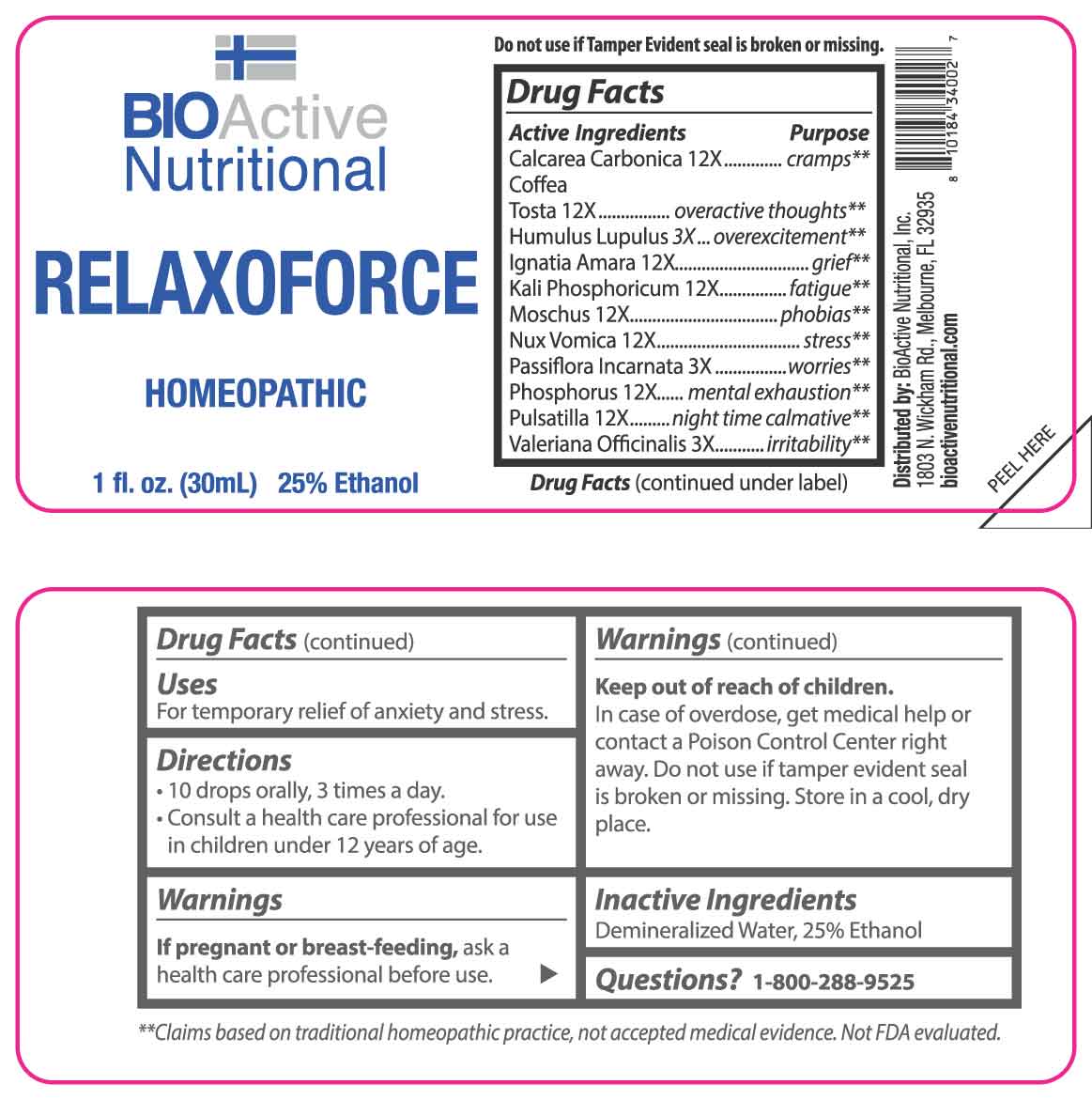 DRUG LABEL: Relaxoforce
NDC: 43857-0545 | Form: LIQUID
Manufacturer: BioActive Nutritional, Inc.
Category: homeopathic | Type: HUMAN OTC DRUG LABEL
Date: 20250401

ACTIVE INGREDIENTS: HOPS 3 [hp_X]/1 mL; PASSIFLORA INCARNATA FLOWERING TOP 3 [hp_X]/1 mL; VALERIAN 3 [hp_X]/1 mL; OYSTER SHELL CALCIUM CARBONATE, CRUDE 12 [hp_X]/1 mL; COFFEA ARABICA SEED, ROASTED 12 [hp_X]/1 mL; STRYCHNOS IGNATII SEED 12 [hp_X]/1 mL; DIBASIC POTASSIUM PHOSPHATE 12 [hp_X]/1 mL; MOSCHUS MOSCHIFERUS MUSK SAC RESIN 12 [hp_X]/1 mL; STRYCHNOS NUX-VOMICA SEED 12 [hp_X]/1 mL; PHOSPHORUS 12 [hp_X]/1 mL; PULSATILLA PRATENSIS WHOLE 12 [hp_X]/1 mL
INACTIVE INGREDIENTS: WATER; ALCOHOL

DRUG FACTS:

ACTIVE INGREDIENTS:

Calcarea Carbonica 12X, Coffea Tosta 12X, Humulus Lupulus 3X, Ignatia Amara 12X, Kali Phosphoricum 12X, Moschus 12X, Nux Vomica 12X, Passiflora Incarnata 3X, Phosphorus 12X, Pulsatilla 12X, Valeriana Officinalis 3X.

PURPOSE:

Calcarea Carbonica - cramps,** Coffea Tosta – overactive thoughts,** Humulus Lupulus - overexcitement,** Ignatia Amara - grief,** Kali Phosphoricum - fatigue,** Moschus - phobias,** Nux Vomica - stress,** Passiflora Incarnata - worries,** Phosphorus – mental exhaustion,** Pulsatilla – night time calmative,** Valeriana Officinalis – irritability**

**Claims based on traditional homeopathic practice, not accepted medical evidence. Not FDA evaluated.

USES:

For temporary relief of anxiety and stress.

WARNINGS:

If pregnant or breast-feeding, ask a health care professional before use.

Keep out of reach of children. In case of overdose, get medical help or contact a Poison Control Center right away.

Do not use if Tamper Evident seal is broken or missing.

Store in cool, dry place.

KEEP OUT OF REACH OF CHILDREN:

In case of overdose, get medical help or contact a Poison Control Center right away.

DIRECTIONS:

• 10 drops orally, 3 times a day.

• Consult a health care professional for use in children under 12 years of age.

INACTIVE INGREDIENTS:

Demineralized Water, 25% Ethanol

QUESTIONS:

Distributed by:
BioActive Nutritional, Inc.
1803 N. Wickham Rd.
Melbourne, FL 32935
bioactivenutritional.com

PACKAGE LABEL DISPLAY:

BIOActive Nutritional

RELAXOFORCE

HOMEOPATHIC

1 FL OZ (30 ml)